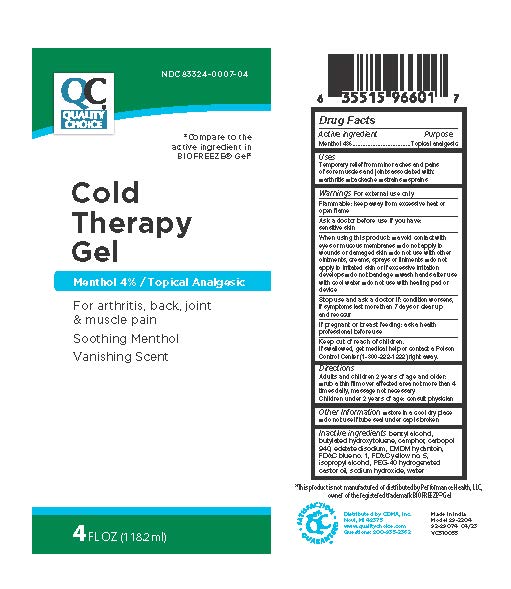 DRUG LABEL: Quality Choice Cold Therapy Gel
NDC: 83324-007 | Form: GEL
Manufacturer: Chain Drug Marketing Association, Inc.
Category: otc | Type: HUMAN OTC DRUG LABEL
Date: 20251229

ACTIVE INGREDIENTS: MENTHOL 40 mg/1 mL
INACTIVE INGREDIENTS: CAMPHOR (NATURAL); CARBOMER 940; BENZYL ALCOHOL; ISOPROPYL ALCOHOL; EDETATE DISODIUM; POLYOXYL 40 HYDROGENATED CASTOR OIL; BUTYLATED HYDROXYTOLUENE; WATER; DMDM HYDANTOIN; SODIUM HYDROXIDE; FD&C BLUE NO. 1; FD&C YELLOW NO. 5

Quality Choice Cold Therapy Gel, 4oz

Warnings

For external use only

Flammable: Keep away from excessive heat or open flame

Ask a doctor before use if you have:

sensitive skin

When using this product:

■ avoid contact with eyes or mucous membranes

■ do not apply to wounds or damaged skin

■ do not use with other ointments, creams, sprays or liniments

■ do not apply to irritated skin or if excessive irritation develops

■ do not bandage ■ wash hands after use with cool water

■ do not use with a heating pad or device

Stop use an ask a doctor if

condition worsens, if symptoms last more than 7 days or clear up and reoccur

If pregnant or breastfeeding:

ask a health professional before use

Keep out of reach of children.

If swallowed, get medical help or contact a Poison Control Center (1-800-222-1222) right away

Directions

adults and children 2 years of age and older:

- rub a thin film over affected area not more than 4 times daily, massage is not necessary

children under 2 years of age: consult a physician

Other Info

■ store in a cool dry place
■ do not use if tube seal under cap is broken

Inactive Ingredients

benzyl alcohol, butylated hydroxytoluene, camphor, carbopol 940, edetate disodium, DMDM hydantoin, FD&C blue no. 1, FD&C yellow no. 5,isopropyl alcohol, PEG-40 hydrogenated castor oil, sodium hydroxide, water

Uses

Temporarily relieves minor aches and pains of muscles and joints associated with:

- arthritis
- backache
- strains
- sprains

Active ingredient

Menthol 4%

Purpose

Topical analgesic